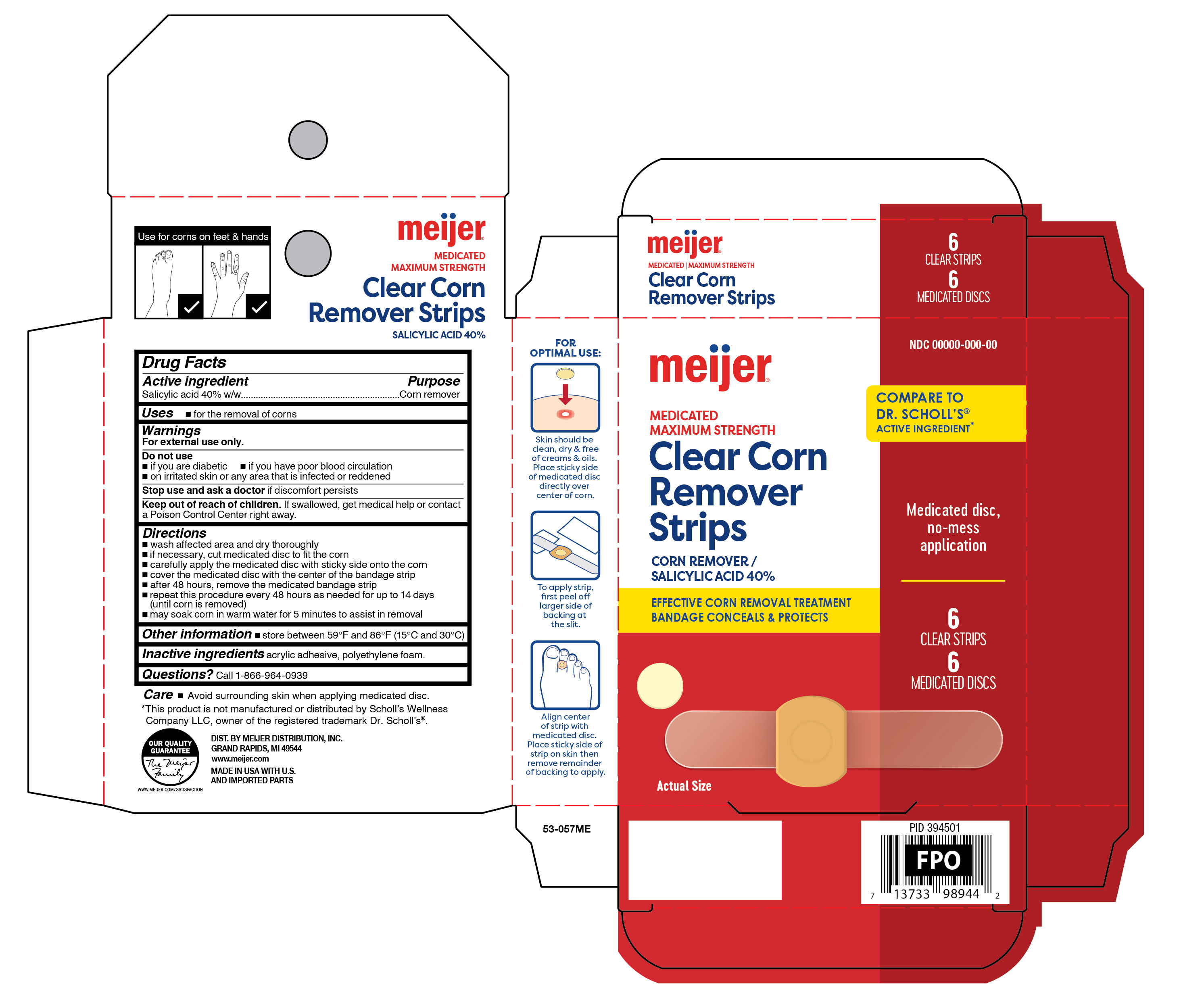 DRUG LABEL: Clear Corn Remover Strips
NDC: 79481-0594 | Form: PATCH
Manufacturer: MEIJER DISTRIBUTION, INC.
Category: otc | Type: HUMAN OTC DRUG LABEL
Date: 20260115

ACTIVE INGREDIENTS: SALICYLIC ACID 40 mg/12 1
INACTIVE INGREDIENTS: VINYL ACETATE; HIGH DENSITY POLYETHYLENE

Meijer Clear Corn Remover Strips

Active ingredient

Salicylic acid 40% w/w

Purpose

Corn remover

Use

- for the removal of corns

Warnings

For external use only.

Do not use

- if you are a diabetic
- if you have poor blood circulation
- on irritated skin or any area that is infected or reddened

Stop use and ask a doctor if

discomfort persists

Keep out of reach of children.

If swallowed, get medical help or contact a Poison Control Center right away.

Directions

- wash affected area and dry area thoroughly.
- if necessary, cut medicated disc to fit the corn.
- carefully apply the medicated with sticky side onto the corn
- cover the medicated disc with the center of the bandage strip.
- after 48 hours, remover the medicated bandage strip.
- repeat this procedure every 48 hours as needed for up to 14 days (until corn is removed).
- may soak corn in warm water for 5 minutes to assist in removal.

Other information

store between 59° and 86°F (15° and 30°C)

Inactive ingredients

acrylic adhesive, polyethylene foam.

Questions?

Call 1-866-964-0939

Principal Display Panel

Meijer

MEDICATED

MAXIMUM STRENGTH

Clear Corn

Remover

Strips

CORN REMOVER/

SALICYLIC ACID 40%

EFFECTIVE CORN REMOVAL TREATMENT

BANDAGE CONCEALS & PROTECTS

Medicated disc, no-mess application

6 CLEAR STRIPS | 6 MEDICATED DISCS